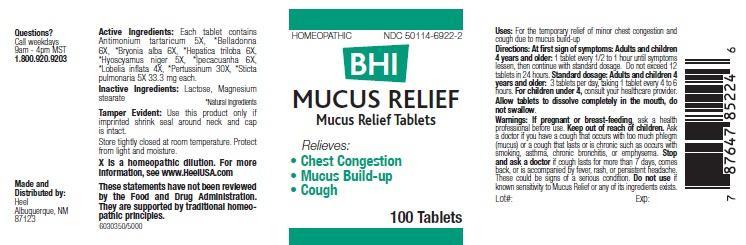 DRUG LABEL: BHI Mucus
NDC: 50114-6922 | Form: TABLET
Manufacturer: Heel Inc
Category: homeopathic | Type: HUMAN PRESCRIPTION DRUG LABEL
Date: 20140414

ACTIVE INGREDIENTS: ANTIMONY POTASSIUM TARTRATE 5 [hp_X]/1 1; ATROPA BELLADONNA 6 [hp_X]/1 1; BRYONIA ALBA ROOT 6 [hp_X]/1 1; ANEMONE AMERICANA 6 [hp_X]/1 1; HYOSCYAMUS NIGER 5 [hp_X]/1 1; IPECAC 6 [hp_X]/1 1; LOBELIA INFLATA 4 [hp_X]/1 1; HUMAN SPUTUM, BORDETELLA PERTUSSIS INFECTED 30 [hp_X]/1 1; LOBARIA PULMONARIA 5 [hp_X]/1 1
INACTIVE INGREDIENTS: LACTOSE; MAGNESIUM STEARATE

BHI Mucus

KEEP OUT OF REACH OF CHILREN

Keep out of reach of children

INDICATIONS AND USAGE

Relieves:

• Chest Congestion

• Mucus Build-up

• Cough

WARNINGS

Warnings: If pregnant or breast-feeding, ask a health professional before use. Keep out of reach of children. Ask a doctor if you have a cough that occurs with too much phlegm (mucus) or a cough that lasts or is chronic such as occurs with smoking, asthma, chronic bronchitis, or emphysema. Stop and ask a doctor if cough lasts for more than 7 days, comes back, or is accompanied by fever, rash, or persistent headache. These could be signs of a serious condition. Do not use if known sensitivity to Mucus Relief or any of its ingredients exists.

DOSAGE

Directions: At first sign of symptoms: Adults and children 4 years and older: 1 tablet every 1/2 to 1 hour until symptoms lessen, then continue with standard dosage. Do not exceed 12 tablets in 24 hours.

Standard dosage: Adults and children 4 years and older: 3 tablets per day, taking 1 tablet every 4 to 6 hours.

For children under 4, consult your healthcare provider.

Allow tablets to dissolve completely in the mouth, do not swallow.

ACTIVE INGREDIENTS

Active Ingredients: Each tablet contains Antimonium tartaricum 5X, *Belladonna 6X, *Bryonia alba 6X, *Hepatica triloba 6X, *Hyoscyamus niger 5X, *Ipecacuanha 6X, *Lobelia inflata 4X, *Pertussinum 30X, *Sticta pulmonaria 5X 33.3 mg each.

*Natural ingredients

INACTIVE INGREDIENTS

Inactive Ingredients: Lactose, Magnesium stearate

PURPOSE

Uses: For the temporary relief of minor chest congestion and cough due to mucus build-up